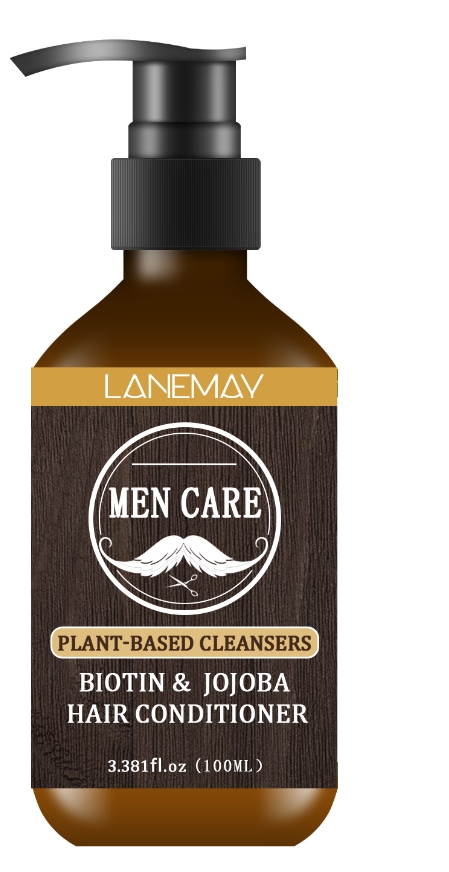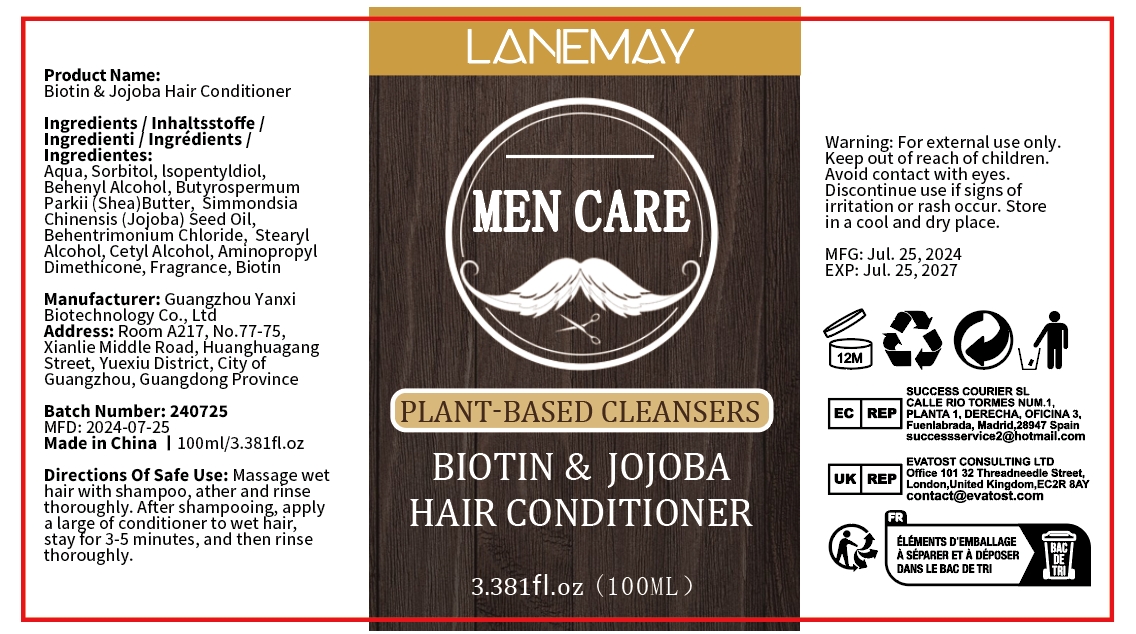 DRUG LABEL: Biotin Jojoba HairConditioner
NDC: 84025-176 | Form: CREAM
Manufacturer: Guangzhou Yanxi Biotechnology Co.. Ltd
Category: otc | Type: HUMAN OTC DRUG LABEL
Date: 20240827

ACTIVE INGREDIENTS: STEARYL ALCOHOL 3 mg/100 mL; SORBITOL 5 mg/100 mL
INACTIVE INGREDIENTS: WATER

DOSAGE AND ADMINISTRATION

Conditioner for nourishing and caring hair

WARNINGS

keep out of children

INACTIVE INGREDIENT

AQUA

INDICATIONS AND USAGE

For daily hair care

keep out of children

PURPOSE

Effectively relieves dry hair and makes hair smooth